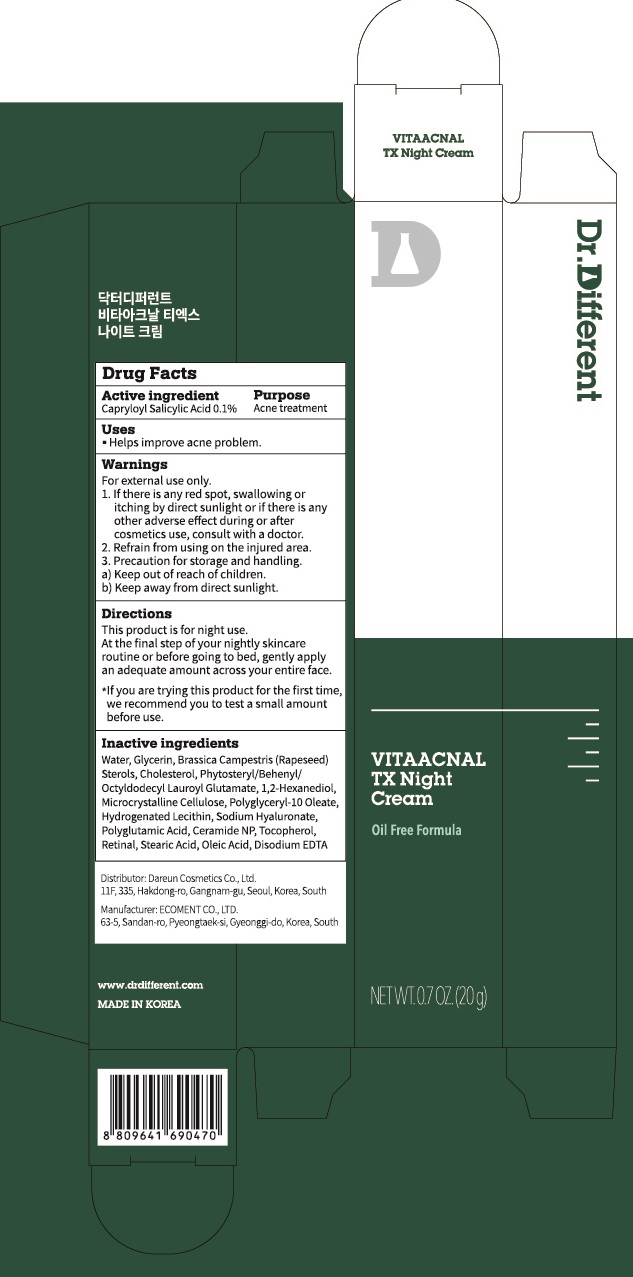 DRUG LABEL: Dr.Different VITAACNAL TX Night
NDC: 81710-070 | Form: CREAM
Manufacturer: Dareun Cosmetics Co., Ltd.
Category: otc | Type: HUMAN OTC DRUG LABEL
Date: 20210412

ACTIVE INGREDIENTS: Capryloyl Salicylic Acid 0.1 g/100 g
INACTIVE INGREDIENTS: WATER; Glycerin; RAPESEED STEROL

ACTIVE INGREDIENT

Capryloyl Salicylic Acid 0.1%

INACTIVE INGREDIENTS

Water, Glycerin, Brassica Campestris (Rapeseed) Sterols, Cholesterol, Phytosteryl/Behenyl/Octyldodecyl Lauroyl Glutamate, 1,2-Hexanediol, Microcrystalline Cellulose, Polyglyceryl-10 Oleate, Hydrogenated Lecithin, Sodium Hyaluronate, Polyglutamic Acid, Ceramide NP, Tocopherol, Retinal, Stearic Acid, Oleic Acid, Disodium EDTA

PURPOSE

Acne treatment

WARNINGS

For external use only.
1. If there is any red spot, swallowing or itching by direct sunlight or if there is any other adverse effect during or after cosmetics use, consult with a doctor.
2. Refrain from using on the injured area.
3. Precaution for storage and handling.
a) Keep out of reach of children.
b) Keep away from direct sunlight.

KEEP OUT OF REACH OF CHILDREN

Uses

■ Helps improve acne problem.

Directions

This product is for night use. At the final step of your nightly skincare routine or before going to bed, gently apply an adequate amount across your entire face.
*If you are trying this product for the first time, we recommend you to test a small amount before use.